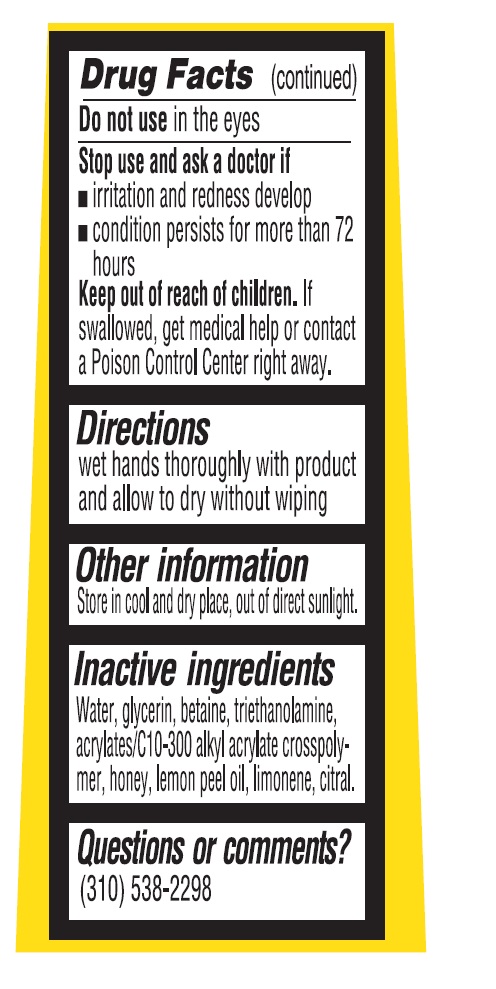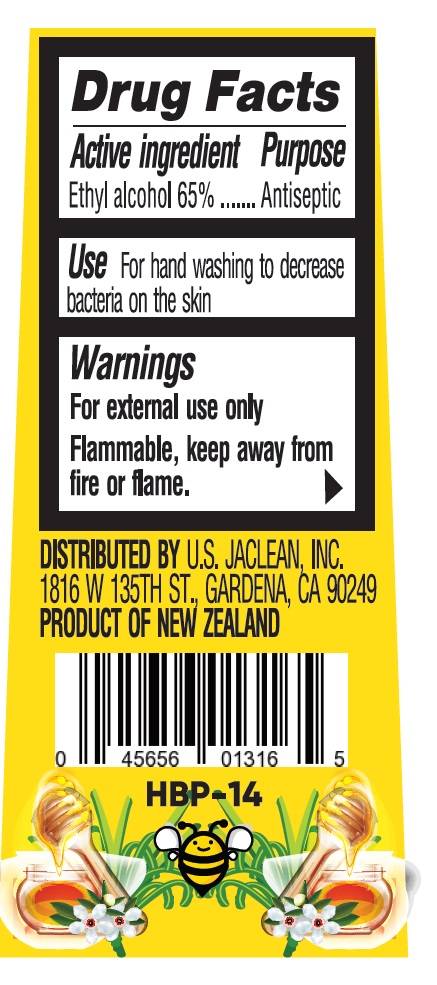 DRUG LABEL: Hand sanitizer
NDC: 70939-004 | Form: GEL
Manufacturer: Dongguang Shuoguo Silicone Products Co., Ltd.
Category: otc | Type: HUMAN OTC DRUG LABEL
Date: 20200516

ACTIVE INGREDIENTS: ALCOHOL 65 mL/100 mL
INACTIVE INGREDIENTS: WATER; BETAINE; GLYCERIN; LIMONENE, (+/-)-; CARBOMER INTERPOLYMER TYPE A (55000 CPS); TROLAMINE; CITRAL; HONEY; LEMON PEEL

70939-004 65% Alcohol Hand Sanitizer

Active ingredient

Alcohol 65%

Purpose

Antiseptic

Use

Use for hand-washing to decrease bacteria on
the skin

Warnings

For etemal use only
Flammabl, keep away from fife and fames
Do not use in the eyes
Stop use and ask a doctor if
1 riation and rednes develop
1 cndition perists for more than72
hours

Keep out of reach of children

Keep out of reach of cilden. if sallowed, get
medical help or contact a Poison ControlCenter
right away

Directions

■wethands trougly with poduotd and alw
todry wthout wiping

INACTIVE INGREDIENT

Wateglyeri, btaine, thanolaminte,nn
ayltasC10-00 ayacylata crspoly
mer, honey, lemon peel ol, limnmene ciral.